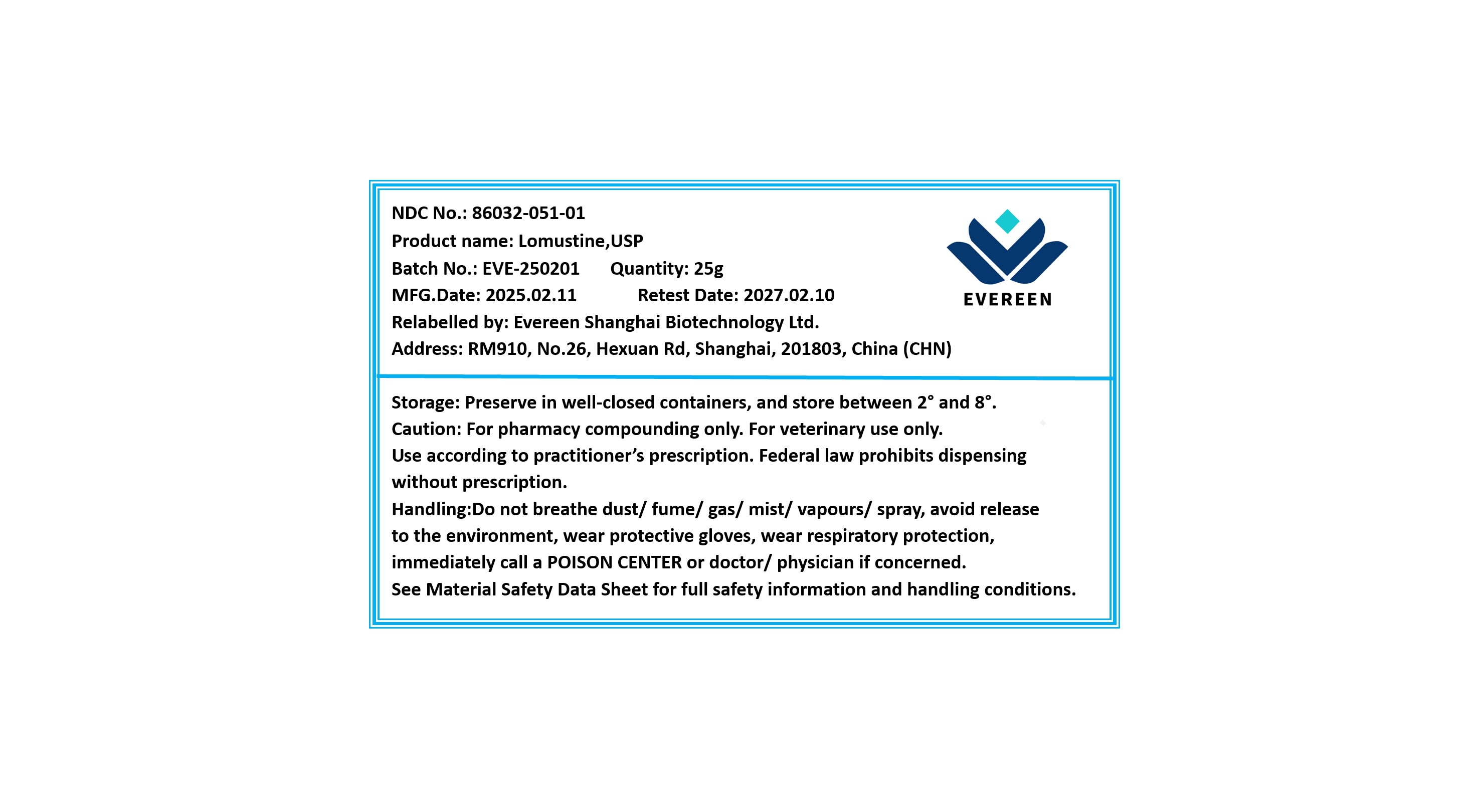 DRUG LABEL: Lomustine
NDC: 86032-051 | Form: POWDER
Manufacturer: Evereen Shanghai Biotechnology Ltd.
Category: other | Type: BULK INGREDIENT - ANIMAL DRUG
Date: 20250604

ACTIVE INGREDIENTS: LOMUSTINE 1 g/1 g

Lomustine